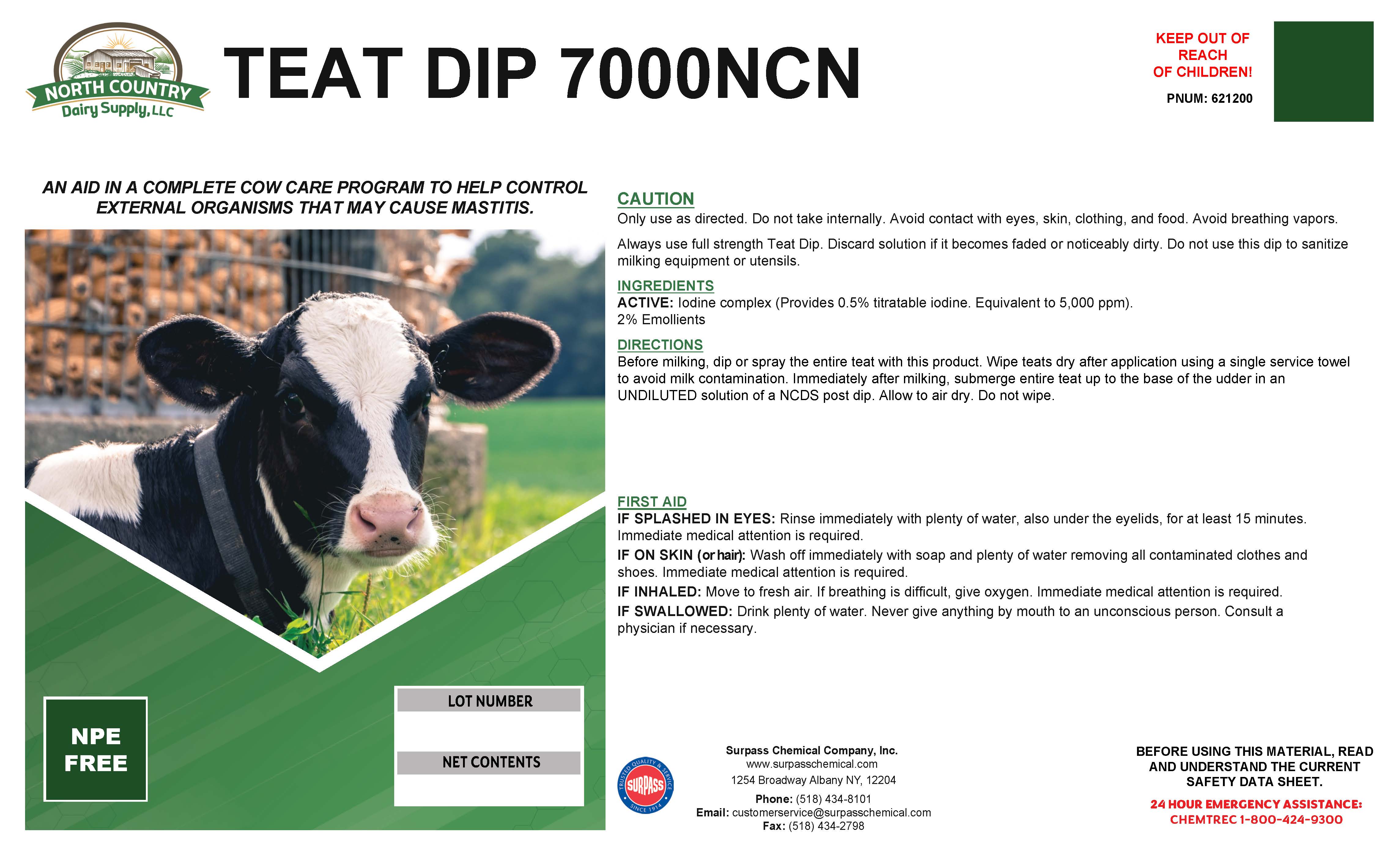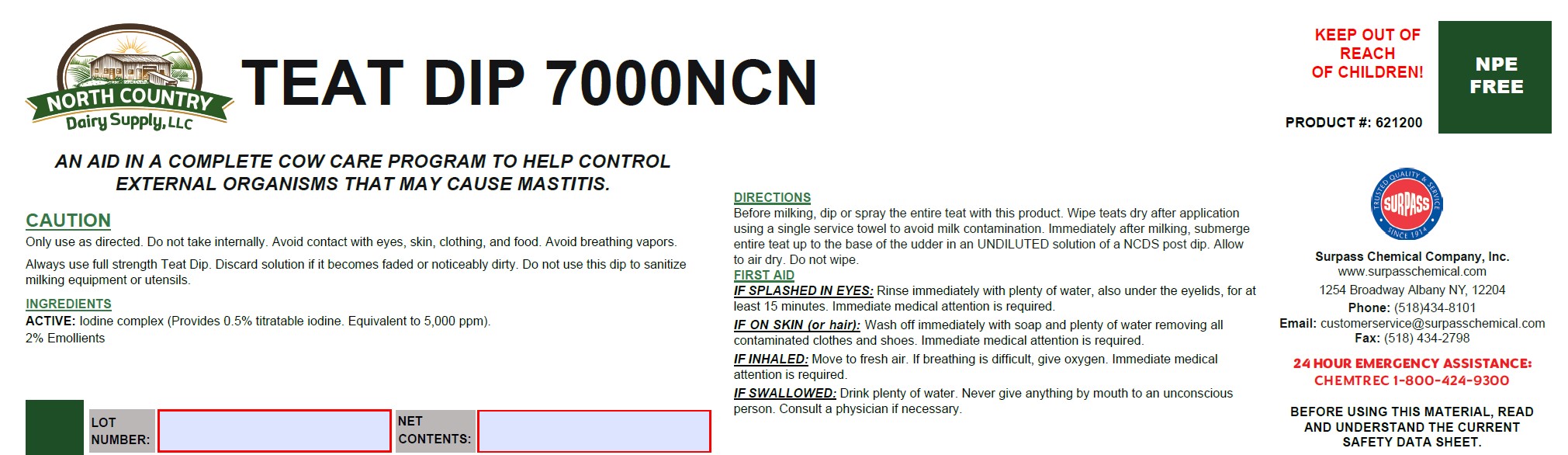 DRUG LABEL: Teat Dip 7000NCN
NDC: 86067-0120 | Form: SOLUTION
Manufacturer: Surpass Chemical Company, Inc.
Category: animal | Type: OTC ANIMAL DRUG LABEL
Date: 20251120

ACTIVE INGREDIENTS: IODINE 0.0232 kg/1 kg
INACTIVE INGREDIENTS: WATER 0.92384 kg/1 kg; C9-11 PARETH-3 0.02881 kg/1 kg; GLYCERIN 0.02005 kg/1 kg; TRISODIUM CITRATE DIHYDRATE 0.0041 kg/1 kg

Teat Dip 7000NCN

DESCRIPTION

TEAT DIP 7000NCN

An aid in a complete cow care program to help control external organisms that may cause mastitis. PNUM: 621200

DIRECTIONS:
Before milking, dip or spray the entire teat with this product. Wipe teats dry after application using a single service towel
to avoid milk contamination. Immediately after milking, submerge entire teat up to the base of the udder in an
UNDILUTED solution of a NCDS post dip. Allow to air dry. Do not wipe.

GENERAL PRECAUTIONS

CAUTION:

Only use as directed. Do not take internally. Avoid contact with eyes, skin, clothing, and food. Avoid breathing vapors.
Always use full strength Teat Dip. Discard solution if it becomes faded or noticeably dirty. Do not use this dip to sanitize
milking equipment or utensils.

ACTIVE INGREDIENT

INGREDIENTS:
ACTIVE: Iodine complex (Provides 0.5% titratable iodine. Equivalent to 5,000 ppm).

2% Emollients

OTHER SAFETY INFORMATION

FIRST AID

IF SPLASHED IN EYES : Rinse immediately with plenty of water, also under the eyelids, for at least 15 minutes. Immediate medical attention is required.
IN CASE OF CONTACT: Wash off immediately with soap and plenty of water removing all contaminated clothes and shoes. Immediate medical attention is required.
IF INHALED: Move to fresh air. If breathing is difficult, give oxygen. Immediate medical attention is required.
IF SWALLOWED: Drink plenty of water. Never give anything by mouth to an unconscious person. Consult a physician if necessary.

KEEP OUT OF
REACH
OF CHILDREN!

Surpass Chemical Company, Inc.
www.surpasschemical.com
Phone: (518) 434-8101

1254 Broadway Albany NY, 12204

Phone: (518) 434-8101

Email: customerservice@surpasschemical.com

Fax: (518) 434-2798

WARNINGS

BEFORE USING THIS MATERIAL, READ AND

UNDERSTAND THE CURRENT SAFETY DATA SHEET

24 HOUR EMERGENCY SERVICE:

CHEMTREC 1-800-434-9300